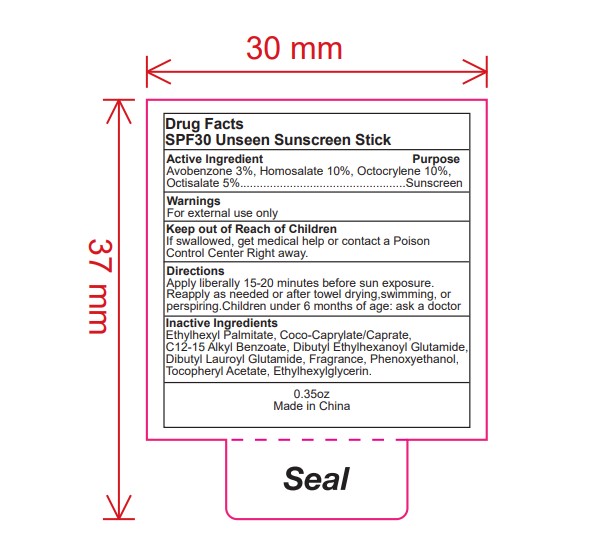 DRUG LABEL: SPF30 unseen sunscreen stick
NDC: 82953-047 | Form: STICK
Manufacturer: Cosmuses Cosmetics (Ningbo) Co., Ltd.
Category: otc | Type: HUMAN OTC DRUG LABEL
Date: 20250728

ACTIVE INGREDIENTS: AVOBENZONE 3 g/100 g; HOMOSALATE 10 g/100 g; OCTOCRYLENE 10 g/100 g; OCTISALATE 5 g/100 g
INACTIVE INGREDIENTS: ETHYLHEXYLGLYCERIN; COCO-CAPRYLATE/CAPRATE; DIBUTYL ETHYLHEXANOYL GLUTAMIDE; ETHYLHEXYL PALMITATE; PHENOXYETHANOL; FRAGRANCE 13576; C12-15 ALKYL BENZOATE; ALPHA-TOCOPHEROL ACETATE; DIBUTYL LAUROYL GLUTAMIDE

SPF 30 Unscented Sunscreen stick

Drug Facts

SPF30 unseen sunscreen stick

Active ingredients

Avobenzone 3%

Homosalate 10%

Octocrylene 10%

Octisalate 5%

Purpose

Sunscreen

Warnings

For external use only.

Keep out of Reach of Children

If swallowed, get medical help or contact a Poison Control Center Right away.

Directions

Apply liberally 15-20 minutes before sun exposure. Reapply as needed or after towel drying, swimming, or perspiring. Children under 6 months of age: ask a doctor

INDICATIONS AND USAGE

Reapply as needed or after towel drying, swimming, or perspiring.

Inactive ingredients

Ethylhexyl Palmitate, Coco-Caprylate/Caprate, C12-15 Alkyl Benzoate, Dibutyl Ethylhexanoyl Glutamide, Dibutyl Lauroyl Glutamide, Fragrance, Phenoxyethanol, Tocopheryl Acetate, Ethylhexylglycerin.